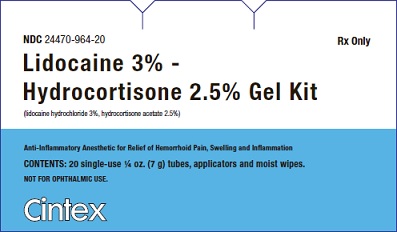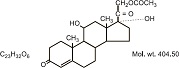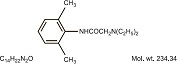 DRUG LABEL: LIDOCAINE HYDROCHLORIDE, HYDROCORTISONE ACETATE
NDC: 24470-964 | Form: GEL
Manufacturer: Cintex Services, LLC
Category: prescription | Type: HUMAN PRESCRIPTION DRUG LABEL
Date: 20240917

ACTIVE INGREDIENTS: LIDOCAINE HYDROCHLORIDE 30 mg/1 g; HYDROCORTISONE ACETATE 25 mg/1 g

Lidocaine 3% - Hydrocortisone 2.5% Gel Kit
(lidocaine hydrochloride 3%, hydrocortisone acetate 2.5%)
Anit-Inflammatory Anesthetic for Relief of Hemorrhoid Pain, Swelling and Inflammation

Rx Only DESCRIPTION:

This product is indicated for the anti-inflammatory and anesthetic relief of itching, pain, soreness, and discomfort due to hemorrhoids, anal fissures, pruritus ani and similar conditions of the anal area.

Each gram contains 30 mg of lidocaine hydrochloride and 25 mg hydrocortisone acetate in a vehicle consisting of: aluminum sulfate, calcium acetate, cetyl alcohol, citric acid, glyceryl stearate (and) PEG-100 stearate, methylparaben, mineral oil, PEG-150 distearate, petrolatum, polycarbophil, propylene glycol, propylparaben, purified water, sodium citrate, sodium hydroxide, stearyl alcohol, xanthan gum.

CLINICAL PHARMACOLOGY:

Mechanism of Action: Product releases lidocaine to stabilize the neuronal membrane by inhibiting the ionic fluxes required for initiation and conduction of impulses, thereby effecting local anesthetic action. Hydrocortisone acetate provides relief of inflammatory and pruritic manifestations of corticosteroid responsive dermatoses. Lidocaine is chemically designated as acetamide, 2-(diethylamino)-N-(2,6-dimethylphenyl), and has the following structure:

Hydrocortisone acetate has a chemical name pregn-4-ene-3, 20-dione, 21-(acetyloxy)- 11,17- dihydroxy-(11ß)-. It has the following structural formula:

Pharmacokinetics: Lidocaine may be absorbed following topical administration to mucous membranes, its rate and extent of absorption depending upon the specific site of application, duration of exposure, concentration, and total dosage. In general, the rate of absorption of local anesthetic agents following topical application occurs most rapidly after intratracheal administration. Lidocaine is also well-absorbed from the gastrointestinal tract, but little intact drug appears in the circulation because of biotransformation in the liver.

Lidocaine is metabolized rapidly by the liver, and metabolites and unchanged drug are excreted by the kidneys. Biotransformation includes oxidative N-dealkylation, ring hydroxylation, cleavage of the amide linkage, and conjugation. N-dealkylation, a major pathway of biotransformation, yields the metabolites monoethylglycinexylidide and glycinexylidide. The pharmacological/toxicological actions of these metabolites are, similar to but less potent than, those of lidocaine. Approximately 90% of lidocaine administered is excreted in the form of various metabolites, and less than 10% is excreted unchanged. The primary metabolite in urine is a conjugate of 4-hydroxy-2, 6-dimethylaniline. The plasma binding of lidocaine is dependent on drug concentration, and the fraction bound decreases with increasing concentration. At concentrations of 1 to 4 g of free base per mL, 60 to 80 percent of lidocaine is protein bound. Binding is also dependent on the plasma concentration of the alpha-1-acid glycoprotein. Lidocaine crosses the blood-brain and placental barriers, presumably by passive diffusion.

Studies of lidocaine metabolism following intravenous bolus injections have shown that the elimination half-life of this agent is typically 1.5 to 2 hours. Because of the rapid rate at which lidocaine is metabolized, any condition that affects liver function may alter lidocaine kinetics. The half-life may be prolonged two-fold or more in patients with liver dysfunction. Renal dysfunction does not affect lidocaine kinetics but may increase the accumulation of metabolites. Factors such as acidosis and the use of CNS stimulants and depressants affect the CNS levels of lidocaine required to produce overt systemic effects. Objective adverse manifestations become increasingly apparent with increasing venous plasma levels above 6 g free base per mL. In the rhesus monkey arterial blood levels of 18-21 g/mL have been shown to be threshold for convulsive activity.

The extent of percutaneous absorption of topical corticosteroids is determined by many factors including the vehicle, the integrity of the epidermal barrier, and the use of occlusive dressings.

Topical corticosteroids can be absorbed from normal intact skin. Inflammation and/or other disease processes in the skin increase percutaneous absorption. Occlusive dressings substantially increase the percutaneous absorption of topical corticosteroids. Thus, occlusive dressings may be a valuable therapeutic adjunct for treatment of resistant dermatoses.

Once absorbed through the skin, topical corticosteroids are handled through pharmacokinetic pathways similar to systemically administered corticosteroids. Corticosteroids are bound to plasma protein in varying degrees. Corticosteroids are metabolized primarily in the liver and are then excreted by the kidneys. Some of the topical corticosteroids and their metabolites are also excreted into the bile.

INDICATIONS:

Product is used for the anti-inflammatory and anesthetic relief of itching, pain, soreness and discomfort due to hemorrhoids, anal fissures, pruritus ani and similar conditions of the anal area.

CONTRAINDICATIONS:

Product should not be used in patients with a history of sensitivity to any of its ingredients or adverse reactions to lidocaine or amide anesthetics, which usually do not cross-react with “caine” ester type anesthetics. If excessive irritation and significant worsening occur, discontinue use and seek the advice of your physician. Product and topical lidocaine should be used cautiously in those with impaired liver function, as well as the very ill or very elderly and those with significant liver disease. Product should be used with caution on patients receiving antiarrhythmic drugs of Class I since the adverse effects are additive and generally synergistic. These products are contraindicated for tuberculous or fungal lesions or skin vaccinia, varicella and acute herpes simplex. Topical corticosteroids are contraindicated in those patients with a history of hypersensitivity to any of the components of the preparation.

WARNINGS: KEEP OUT OF REACH OF CHILDREN.

Product, applicators and moist wipes could harm small children if chewed or swallowed.

Methemoglobinemia

Cases of methemoglobinemia have been reported in association with local anesthetic use. Although all patients are at risk for methemoglobinemia, patients with glucose-6-phosphate dehydrogenase deficiency, congenital or idiopathic methemoglobinemia, cardiac or pulmonary compromise, infants under 6 months of age, and concurrent exposure to oxidizing agents or their metabolites are more susceptible to developing clinical manifestations of the condition. If local anesthetics must be used in these patients, close monitoring for symptoms and signs of methemoglobinemia is recommended.

Signs and symptoms of methemoglobinemia may occur immediately or may be delayed some hours after exposure and are characterized by a cyanotic skin discoloration and abnormal coloration of the blood. Methemoglobin levels may continue to rise; therefore, immediate treatment is required to avert more serious central nervous system and cardiovascular adverse effects, including seizures, coma, arrhythmias, and death. Discontinue the use of this product and any other oxidizing agents. Depending on the severity of the symptoms, patients may respond to supportive care, i.e., oxygen therapy, hydration. More severe symptoms may require treatment with methylene blue, exchange transfusion, or hyperbaric oxygen.

Drug Interactions: Patients that are administered local anesthetics may be at increased risk of developing methemoglobinemia when concurrently exposed to the following oxidizing agents: nitrates/nitrites (nitroglycerin, nitroprusside, nitric oxide, nitrous oxide); local anesthetics (benzocaine, lidocaine, bupivacaine, mepivacaine, tetracaine, prilocaine, procaine, articaine, ropivacaine); antineoplastic agents (cyclophosphamide, flutamide, rasburicase, ifosfamide, hydroxyurea); antibiotics (dapsone, sulfonamides, nitrofurantoin, para-aminosalicylic acid); antimalarials (chloroquine, primaquine); anticonvulsants (phenytoin, sodium valproate, phenobarbital); other drugs (acetaminophen, metoclopramide, sulfa drugs (i.e., sulfasalazine), quinine).

Patient Counseling Information: Inform patients that use of local anesthetics may cause methemoglobinemia, a serious condition that must be treated promptly. Advise patients or caregivers to stop use and seek immediate medical attention if they or someone in their care experience the following signs or symptoms: pale, gray, or blue colored skin (cyanosis); headache; rapid heart rate; shortness of breath; lightheadedness; or fatigue.

Topical formulations of lidocaine may be absorbed to a greater extent through mucous membranes and abraded, fissured or irritated skin than through intact skin. Product should not be ingested or applied into the mouth, inside of the nose or in the eyes. Product should not be used in the ears. Any situation where lidocaine penetrates beyond the tympanic membrane into the middle ear is contraindicated because of ototoxicity associated with lidocaine observed in animals when instilled in the middle ear. Product should not come into contact with the eye or be applied into the eye because of the risk of severe eye irritation and the loss of eye surface sensation which reduces protective reflexes and can lead to corneal irritation and possibly abrasion. If eye contact occurs, rinse out the eye immediately with saline or water and protect the eye surface until sensation is restored.

PRECAUTIONS: FOR EXTERNAL USE ONLY. NOT FOR OPHTHALMIC USE.

If irritation or sensitivity occurs or infection appears, discontinue use and institute appropriate therapy. If extensive areas are treated, the possibility of systemic absorption exists. Systemic absorption of topical steroids has produced reversible hypothalamic pituitary-adrenal (HPA) axis suppression, manifestations of Cushing’s syndrome, hyperglycemia, and glycosuria in some patients. Conditions which augment systemic absorption include the application of the more potent steroids, use over large surface areas, prolonged use, and the addition of occlusive dressings. Therefore, patients receiving a large dose of potent topical steroids applied to a large surface area, or under an occlusive dressing, should be evaluated periodically for evidence of HPA axis suppression. If noted, an attempt should be made to withdraw the drug to reduce the frequency of application, or to substitute a less potent steroid.

Recovery of the HPA axis function is generally prompt and complete upon discontinuation of the drug. Infrequently, signs and symptoms of steroid withdrawal may occur, requiring supplemental systemic corticosteroids. Children may absorb proportionately larger amounts of topical corticosteroids and thus be more susceptible to systemic toxicity. If irritation develops, topical steroids should be discontinued and appropriate therapy instituted.

In the presence of dermatological infections, the use of an appropriate antifungal or antibacterial agent should be instituted. If a favorable response does not occur promptly, the corticosteroid should be discontinued until the infection has been adequately controlled.

Carcinogenesis, Mutagenesis and Impairment of Fertility: Long-term animal studies have not been performed to evaluate the carcinogenic potential or the effect on fertility of topical corticosteroids. Studies to determine mutagenicity with prednisolone and hydrocortisone have revealed negative results. Studies of lidocaine in animals to evaluate the carcinogenic and mutagenic potential of the effect on fertility have not been conducted.

Pregnancy: Category C. Reproduction studies have been performed for lidocaine in rats at doses up to 6.6 times the human dose and have revealed no evidence of harm to the fetus caused by lidocaine. There are, however, no adequate and well-controlled studies in pregnant women. Animal reproduction studies are not always predictive of human response. General consideration should be given to this fact before administering lidocaine to women of childbearing potential, especially during early pregnancy when maximum organogenesis takes place. Corticosteroids are generally teratogenic in laboratory animals when administered systemically at relatively low dosage levels. The more potent corticosteroids have been shown to be teratogenic after dermal application in laboratory animals. There are no adequate and well controlled studies in pregnant women on teratogenic effects from topically applied corticosteroids. Therefore, topical corticosteroids should be used during pregnancy only if the potential benefit justifies the potential risk to the fetus. Drugs of this class should not be used extensively on pregnant patients, in large amounts, or for prolonged periods of time.

Nursing Mothers: Lidocaine is excreted in human milk. The clinical significance of this observation is unknown. Caution should be exercised when lidocaine is administered to a nursing woman.

Pediatric Use: Safety and efficacy in children have not been established.

ADVERSE REACTIONS:

During, immediately, or following application of product, there may be transient stinging or burning from open areas of skin, or transient blanching (lightening), or erythema (redness) of the skin.

DOSAGE AND ADMINISTRATION:

Apply product to the affected area(s) twice daily or as directed by a physician. Product should not be used in excess of recommendations or for prolonged use in the anal canal. If the condition does not respond to repeated courses of product or should worsen, discontinue use and seek the advice of your physician.

Patient Directions for Rectal Administration: Remove moist wipe from box, tear open the package, gently clean the affected area and discard moist wipe. (Note: The moist wipe does not contain any of the prescribed active ingredients.) The cap and foil seal should be removed from the tube and the applicator tip firmly screwed onto the end of the tube and tightened. (Do not over tighten.) While holding the tube, gently squeeze the tube until a small amount of gel comes out of the applicator openings. This will lubricate the applicator tip. Gently insert the applicator tip into anal area. Continue squeezing the body of the tube as you move it around the areas of discomfort, and lastly, around and in the anal opening (if directed by physician). Do not completely insert the applicator and tube into the anus or insert deep into the rectum. Do not insert a loose applicator tip into the anus or rectum. Once application is completed, the tube and applicator tip should be gently removed and discarded.

STORAGE:

Store at 20°C to 25°C (68°F to 77°F), excursions permitted between 15°C to 30°C (between 59°F to 86°F). Brief exposure to temperatures up to 40°C (104°F) may be tolerated provided the mean kinetic temperature does not exceed 25°C (77°F); however, such exposure should be minimized.

NOTICE: Protect from freezing and excessive heat.

HOW SUPPLIED:

Each carton, NDC 24470-964-20, contains 20 single-use ¼ oz (7 g) tubes of Lidocaine 3% - Hydrocortisone 2.5% Gel, 20 applicators, and 20 moist wipes. Each tube is a unit of use - not for individual sale. Discard tube, applicator, and wipe after use.

To report a serious adverse event or obtain product information, call 1-855-899-4237.

KEEP THIS AND ALL MEDICATIONS OUT OF THE REACH OF CHILDREN. All prescriptions using this product shall be pursuant to state statutes as applicable. This is not an Orange Book product. This product may be administered only under a physician’s supervision. There are no implied or explicit claims on the therapeutic equivalence.

Manufactured for:

Cintex Services, LLC

9330 LBJ Freeway, Suite 900

Dallas, TX 75243

2400225 [00] Rev. 09/2024